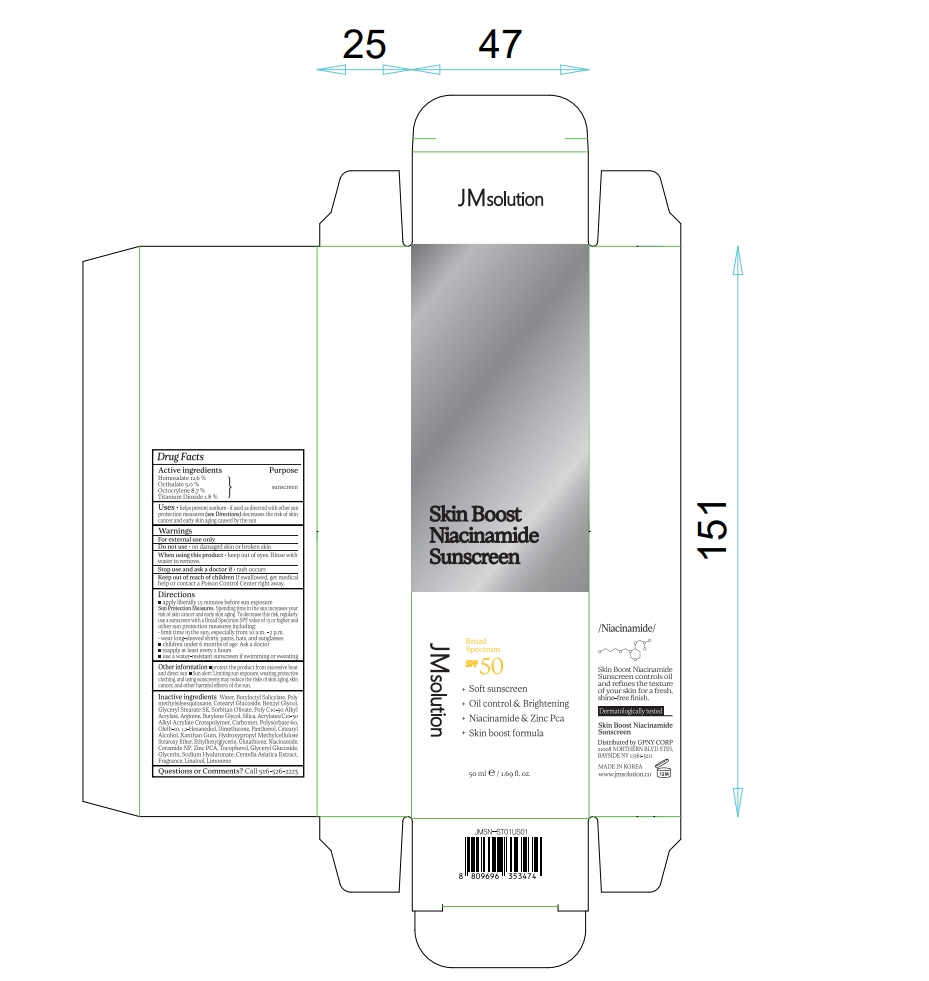 DRUG LABEL: JMSOLUTION SKIN BOOST NIACINAMIDE SUNSCREEN
NDC: 84754-051 | Form: CREAM
Manufacturer: GPNY CORP
Category: otc | Type: HUMAN OTC DRUG LABEL
Date: 20241111

ACTIVE INGREDIENTS: OCTOCRYLENE 4.35 g/50 mL; OCTISALATE 2.5 g/50 mL; TITANIUM DIOXIDE 0.9 g/50 mL; HOMOSALATE 6.3 g/50 mL
INACTIVE INGREDIENTS: BUTYLENE GLYCOL; XANTHAN GUM; ETHYLHEXYLGLYCERIN; PANTHENOL; ETHYLENE GLYCOL MONOBENZYL ETHER; CERAMIDE NP; CETEARYL GLUCOSIDE; DIMETHICONE; TOCOPHEROL; NIACINAMIDE; WATER; SORBITAN OLIVATE; POLYSORBATE 60; OLETH-10; GLUTATHIONE; CENTELLA ASIATICA TRITERPENOIDS; ARGININE; GLYCERYL STEARATE SE; ZINC PIDOLATE; GLYCERIN; CARBOMER HOMOPOLYMER, UNSPECIFIED TYPE; 1,2-HEXANEDIOL; LINALOOL, (+/-)-; POLYMETHYLSILSESQUIOXANE (4.5 MICRONS); CETOSTEARYL ALCOHOL; LIMONENE, (+)-; BUTYLOCTYL SALICYLATE

JMSOLUTION SKIN BOOST NIACINAMIDE SUNSCREEN

Active ingredients

Homosalate 12.6 %
Octisalate 5.0 %
Octocrylene 8.7 %
Titanium Dioxide 1.8 %

Purpose

sunscreen

Uses

• helps prevent sunburn • if used as directed with other sun protection measures (see Directions) decreases the risk of skin cancer and early skin aging caused by the sun

Warnings

For external use only

Do not use

• on damaged skin or broken skin

When using this product

• keep out of eyes. Rinse with water to remove.

Stop use and ask a doctor if

• rash occurs

Keep out of reach of children

If swallowed, get medical help or contact a Poison Control Center right away.

Directions

■ apply liberally 15 minutes before sun exposure
Sun Protection Measures. Spending time in the sun increases your risk of skin cancer and early skin aging. To decrease this risk, regularly use a sunscreen with a Broad Spectrum SPF value of 15 or higher and other sun protection measures including:
• limit time in the sun, especially from 10 a.m. - 2 p.m.
• wear long-sleeved shirts, pants, hats, and sunglasses
■ children under 6 months of age: Ask a doctor
■ reapply at least every 2 hours
■ use a water-resistant sunscreen if swimming or sweating

Other information

■ protect the product from excessive heat and direct sun ■ Sun alert: Limiting sun exposure, wearing protective clothing, and using sunscreens may reduce the risks of skin aging, skin cancer, and other harmful effects of the sun.

Inactive ingredients

Water, Butyloctyl Salicylate, Polymethylsilsesquioxane, Cetearyl Glucoside, Benzyl Glycol, Glyceryl Stearate SE, Sorbitan Olivate, Poly C10-30 Alkyl Acrylate, Arginine, Butylene Glycol, Silica, Acrylates/C10-30 Alkyl Acrylate Crosspolymer, Carbomer, Polysorbate 60, Oleth-10, 1,2-Hexanediol, Dimethicone, Panthenol, Cetearyl Alcohol, Xanthan Gum, Hydroxypropyl Methylcellulose Stearoxy Ether, Ethylhexylglycerin, Glutathione, Niacinamide, Ceramide NP, Zinc PCA, Tocopherol, Glyceryl Glucoside, Glycerin, Sodium Hyaluronate, Centella Asiatica Extract, Fragrance, Linalool, Limonene